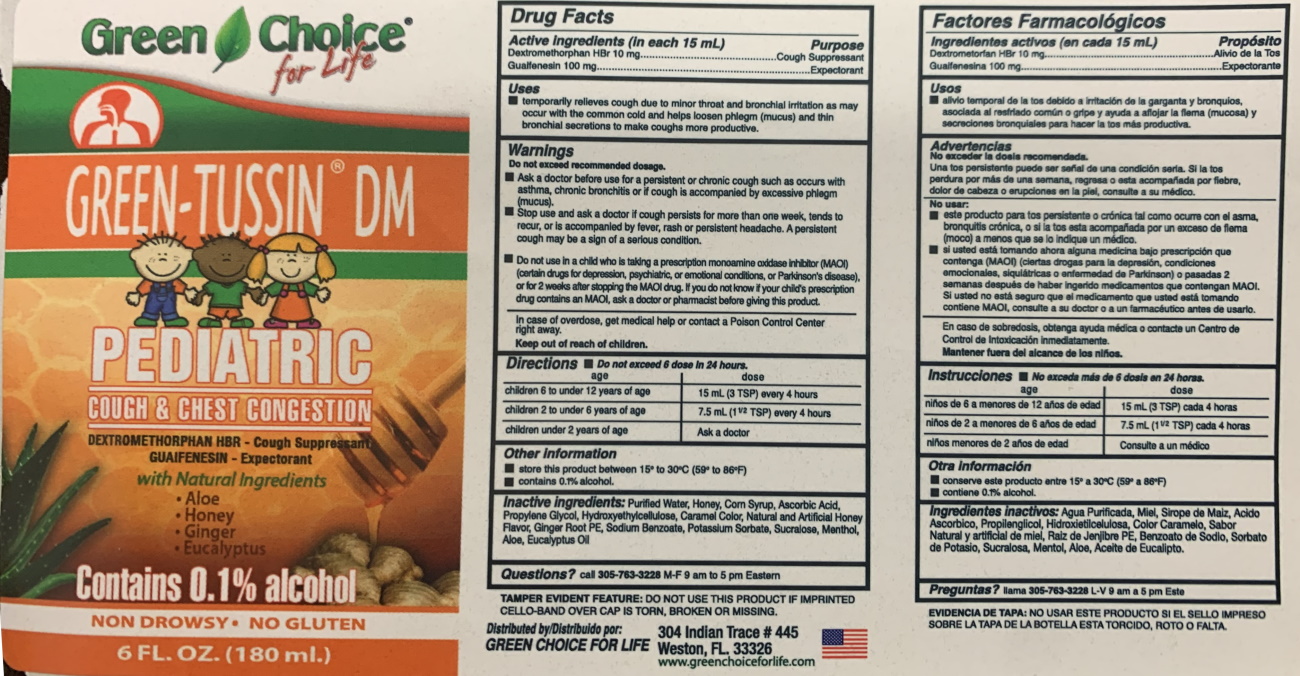 DRUG LABEL: Green Tussin
NDC: 55287-112 | Form: LIQUID
Manufacturer: Green Choice for Life Pediatric
Category: otc | Type: HUMAN OTC DRUG LABEL
Date: 20210102

ACTIVE INGREDIENTS: Guaifenesin 100 mg/15 mL; DEXTROMETHORPHAN HYDROBROMIDE 10 mg/15 mL
INACTIVE INGREDIENTS: ASCORBIC ACID; ALOE; GINGER; CAT'S CLAW; METHYLPARABEN; PROPYLPARABEN; SODIUM BENZOATE; PROPYLENE GLYCOL; POTASSIUM SORBATE; EUCALYPTUS OIL; PEPPERMINT; MENTHOL; ONION; GARLIC; SUCRALOSE; CARAMEL; HONEY; CORN SYRUP; WATER

Active Ingredients (in each 15 mL)

Dextromethorphan HBr 10mg.............Cough Suppressant

Guaifenesin 100mg.........................................Expectorant

PURPOSE

Cough Suppressant

Expectorant

Uses

- temporarily relieves cough due to minor throat and bronchial irritation as may occur with the common cold and helps loosen phlegm (mucus) and thin bronchial sections to make coughs more productive.

Warnings

Do not exceed recommended dosage.

In case of overdose, get medical help or contact a Posion Control Center right away.

Do not use

- On child taking a prescription monoamine oxidase inhibitor (MAOI) (certain drugs for depression, psychiatric, or emotional conditions, or Parkinson’s Disease), or for 2 weeks after stopping the MAOI drug. If you do not know if your child's prescription drug contains an MAOI, ask your doctor or pharmacist before taking this product.

Ask Doctor

- Before use for a persistent or chronic cough, such as occurs with asthma, chronic bronchitis or if cough is accompanied by excessive phlegm (mucus)

Stop Use

- if cough persists for more than one week, tends to recur, or is accompanied by fever, rash or persistent headache. A persisten coug may be a sign of a serious condition.

PREGNANCY OR BREAST FEEDING

If pregnant or breast-feeding, ask health professional before use.

Incase of accidental overdose, get medical help or contact a Poison Control Center right away.

Keep out of reach of children.

DOSAGE AND ADMINISTRATION

- Do not exceed 6 doses in 24 hours

children 6 to under 12 Years of age or more.............15mL ((3 tsp) every 4 hours

children 2 to under 6 Years of age or more.............7.5mL ((1 1/2 tsp) every 4 hours

children under 2 years of age..............................ask a doctor

Other information

- store this product between 15° to 30°C (59° to 86°F)
- Contains 0.1% of alcohol

INACTIVE INGREDIENT

Inactive Ingredients aloe, ascorbic acid, caramel color, cat's claw extract, corn syrup, ethyl alcohol, eucalyptus oil, garlic FE, ginger root FE, honey, menthol, methyl paraben, onion FE, peppermint spirits, potassium sorbate, propylene glycol, propyl paraben, sodium benzoate, sucralose

QUESTIONS

Questions? call 305-763-3228 M-F 9 am to 5 pm Eastern